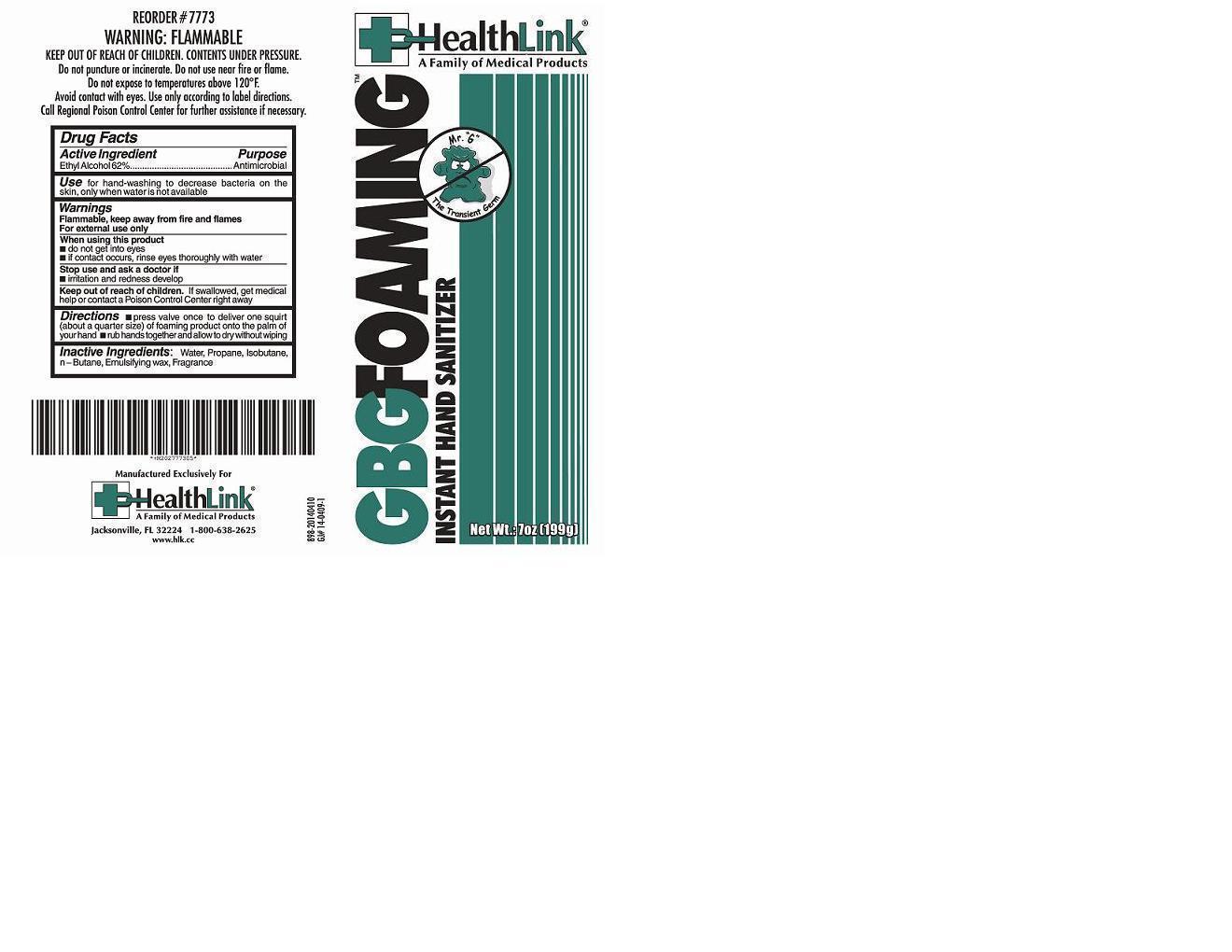 DRUG LABEL: GBG
NDC: 63843-898 | Form: AEROSOL, FOAM
Manufacturer: HealthLink
Category: otc | Type: HUMAN OTC DRUG LABEL
Date: 20180207

ACTIVE INGREDIENTS: ALCOHOL 0.62 g/1 g
INACTIVE INGREDIENTS: WATER; CETOSTEARYL ALCOHOL; POLYSORBATE 60; BUTANE; PROPANE

GBGFOAMING™
INSTANT HAND SANITIZER

Drug Facts

Active Ingredient

Ethyl Alcohol 62%

Purpose

Antimicrobial

Use

for hand-washing to decrease bacterial on the skin, only when water is not available

Warnings

Flamable, keep away from fire and flames

For external use only

When using this product

- do not get into eyes
- if contact occurs, rinse eyes thoroughly with water

Stop use and ask a doctor if

- irritation and redness develop

Keep out of reach of children. If swallowed, get medical help or contact a Poison Control Center right away

Directions

- press valve once to deliver one squirt (about a quarter size) of foaming product onto the palm of your hand
- rub hands together and allow to dry without wiping

Inactive Ingredients

Water, Propane, Isobutane, n-Butane, Emulsifying wax, Fragrance

Manufactured Exclusively For

HealthLink®
A Family of Medical Products

Jacksonville, FL 32224 1-800-638-2625